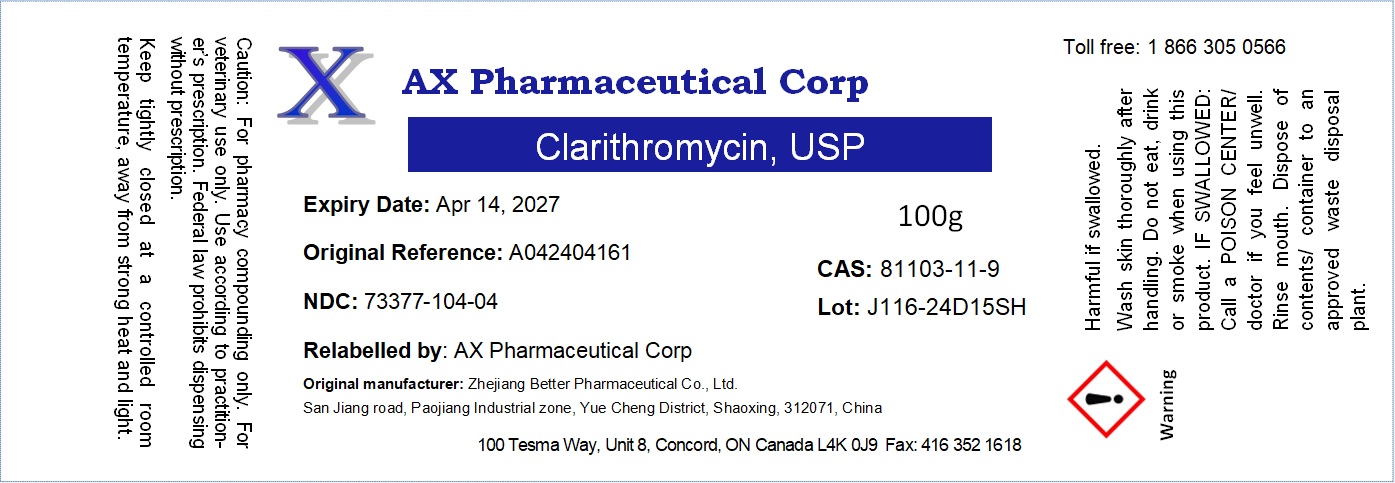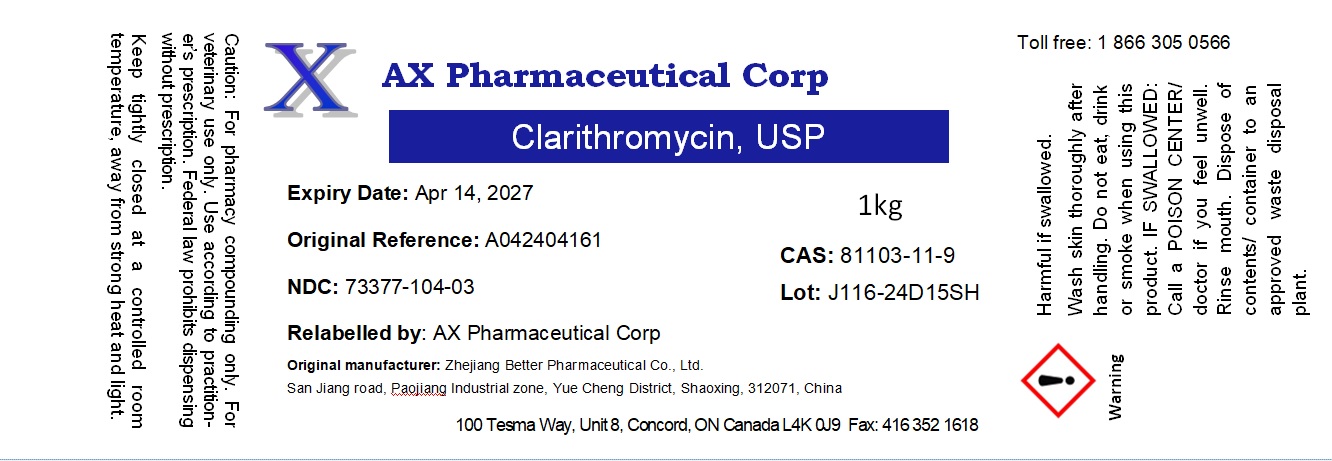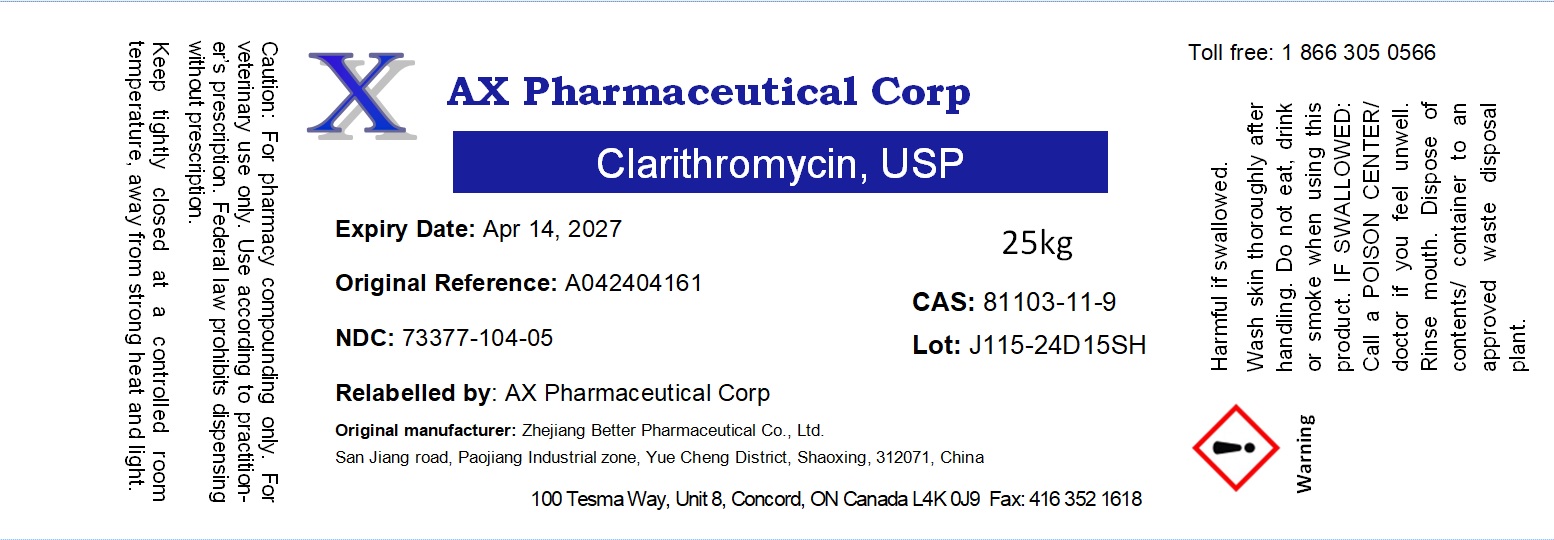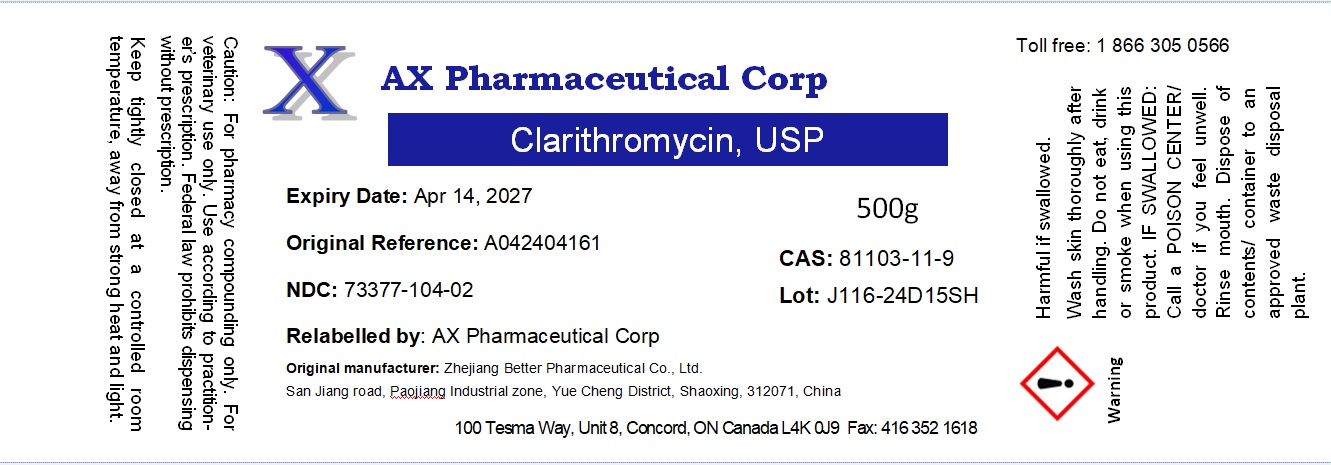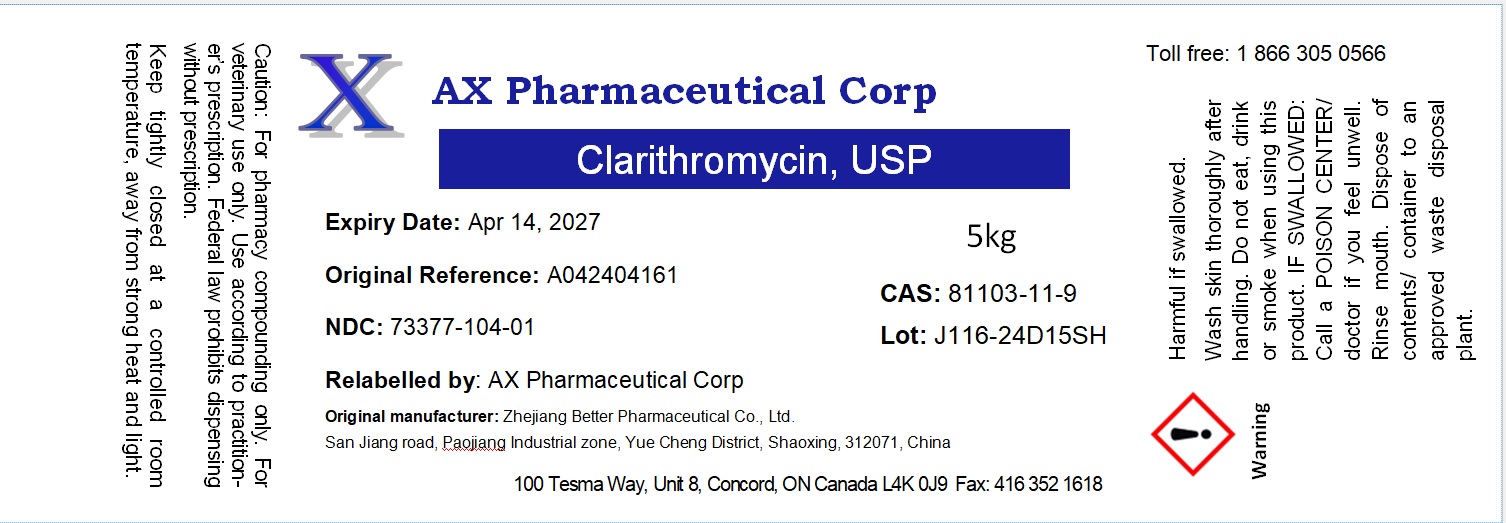 DRUG LABEL: Clarithromycin
NDC: 73377-104 | Form: POWDER
Manufacturer: AX Pharmaceutical Corp
Category: other | Type: BULK INGREDIENT - ANIMAL DRUG
Date: 20241022

ACTIVE INGREDIENTS: CLARITHROMYCIN 1 kg/1 kg

Clarithromycin